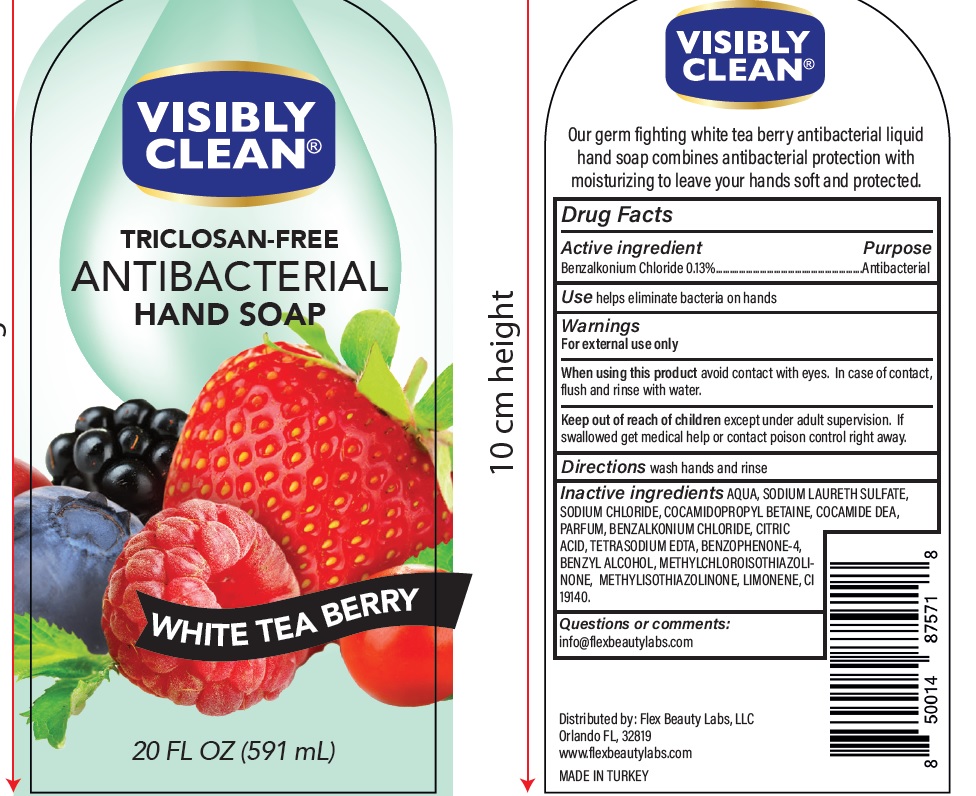 DRUG LABEL: Antibacterial
NDC: 72308-020 | Form: LIQUID
Manufacturer: Flex Beauty Labs
Category: otc | Type: HUMAN OTC DRUG LABEL
Date: 20200730

ACTIVE INGREDIENTS: BENZALKONIUM CHLORIDE 1.3 mg/1 mL
INACTIVE INGREDIENTS: WATER; SODIUM LAURETH SULFATE; COCAMIDOPROPYL BETAINE; COCO DIETHANOLAMIDE; SODIUM CHLORIDE; SULISOBENZONE; EDETATE SODIUM; METHYLCHLOROISOTHIAZOLINONE; METHYLISOTHIAZOLINONE; BENZYL ALCOHOL; CITRIC ACID MONOHYDRATE; FD&C YELLOW NO. 5; LIMONENE, (+)-

Antibacterial -Visibly Clean Triclosan Free Hand Soap White tea Berry

Purpose - Antibacterial

INDICATIONS AND USAGE

Use help eliminate bacteria on hands

Warnings

For external use only

Stop use and ask a doctor if irritation or redness develops

When using this product

Avoid contact with eyes.In case of contact, flush and rinse with water.

Keep out of reach of children

Except under adult supervision.

If swallowed get medical help or contact posion control right away.

Directions

Wash hands and rinse

INACTIVE INGREDIENT

Water, Sodium Laureth Sulfate, Cocamidopropyl Betaine, Sodium Chloride, Citric Acid, Coamide DEA, Parfum, Tetrasodium EDTA, Methylchloroisothiazolinone, Methylisothiazolinone, Benzophenone-4 ,Cl 19140, Limonene.

ACTIVE INGREDIENT

Benzalkonium Chloride - 0.13%